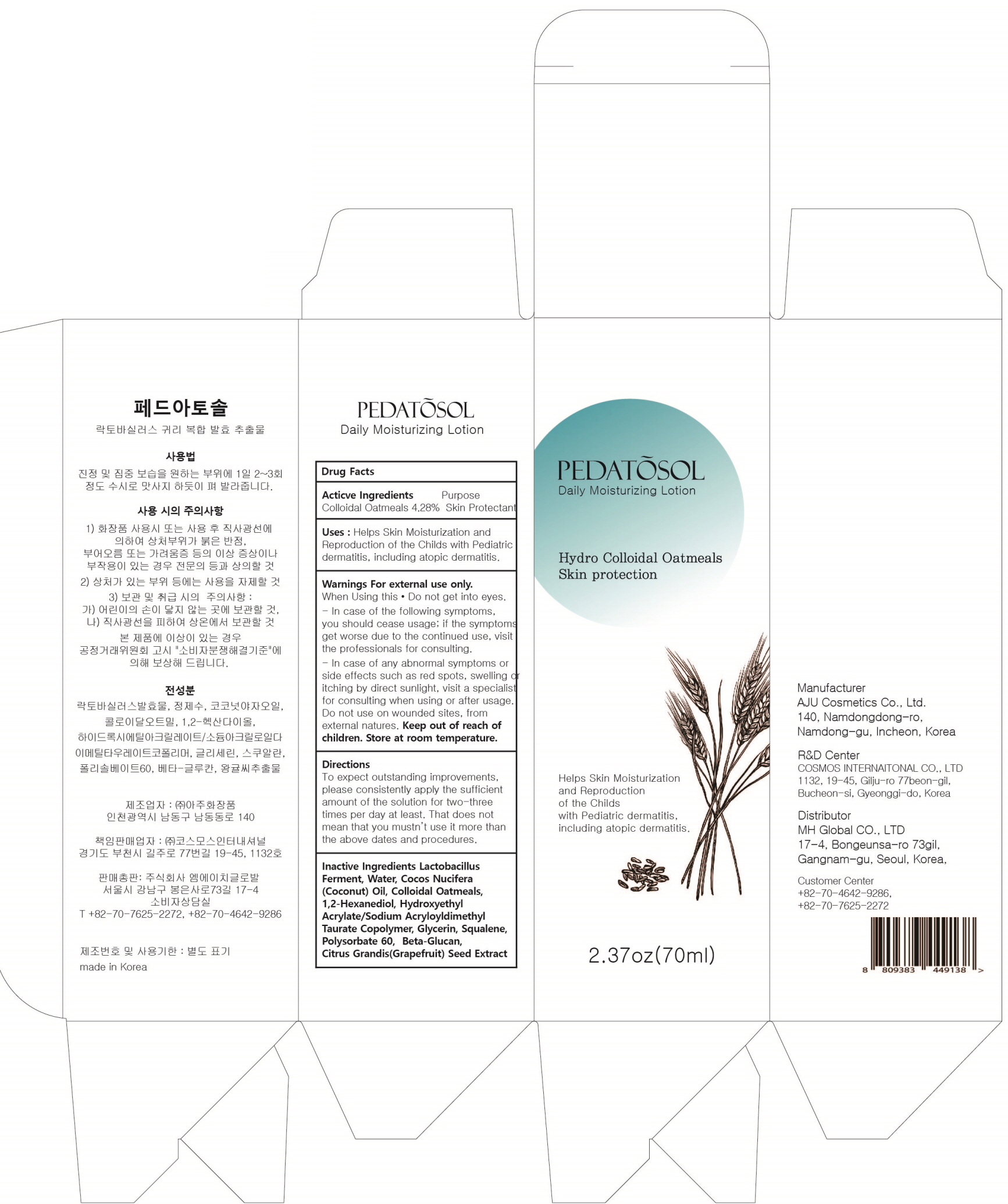 DRUG LABEL: PEDATOSOL
NDC: 73113-010 | Form: SOLUTION
Manufacturer: Mh Global Co., Ltd.
Category: otc | Type: HUMAN OTC DRUG LABEL
Date: 20190823

ACTIVE INGREDIENTS: Oatmeal 2.99 g/70 mL
INACTIVE INGREDIENTS: Water; Glycerin

ACTIVE INGREDIENT

Active ingredients: Colloidal Oatmeals 4.28 %

INACTIVE INGREDIENT

Inactive ingredients:

Lactobacillus Ferment Extract, Water, Cocos Nucifera (Coconut) Oil, 1,2-Hexanediol, Glycerin, Hydroxyethyl Acrylate/Sodium Acryloyldimethyl Taurate Copolymer, Squalene, Polysorbate 60, Beta-Glucan, Citrus Grandis (Grapefruit) Seed Extract

PURPOSE

Purpose: Skin Protectant

WARNINGS

For external use only.

When Using this • Do not get into eyes. - In case of the following symptoms, you should cease usage; if the symptoms get worse due to the continued use, visit the professionals for consulting
- In case of any abnormal symptoms or side effects such as red spots, swelling or itching by direct sunlight, visit a specialist for consulting when using or after usage. Do not use on wounded sites, from external natures. Keep out of reach of children. Store at room temperature.

KEEP OUT OF REACH OF CHILDREN

Uses

Helps Skin Moisturization and Reproduction of the Childs with Pediatric dermatitis, including atopic dermatitis.

Directions

To expect outstanding improvements, please consistently apply the sufficient amount of the solution for two-three times per day at least. That does not mean that you mustn’t use it more than the above dates and procedures.